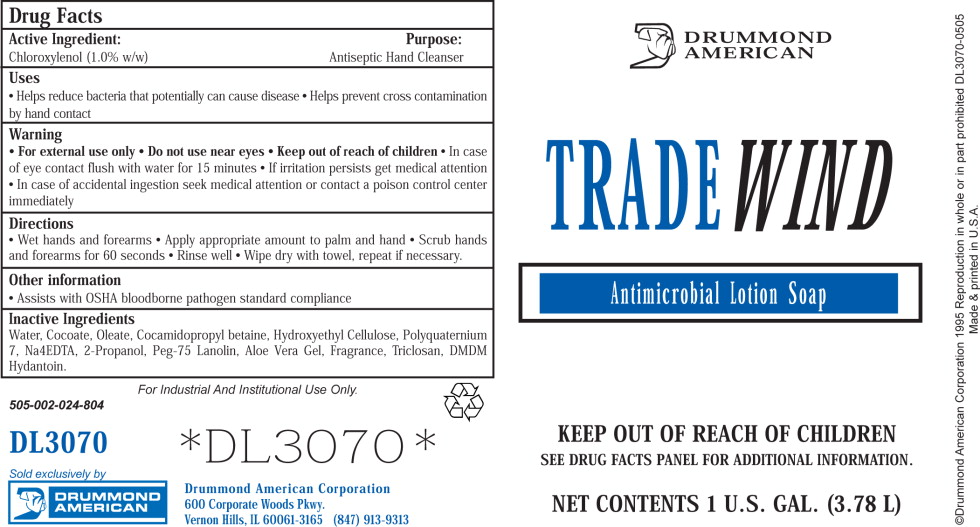 DRUG LABEL: Drummond American Trade Wind Antimicrobial
NDC: 62428-505 | Form: LIQUID
Manufacturer: Lawson Products, Inc.
Category: otc | Type: HUMAN OTC DRUG LABEL
Date: 20100801

ACTIVE INGREDIENTS: chloroxylenol 10.22 g/1000 mL
INACTIVE INGREDIENTS: water; potassium oleate; cocamidopropyl betaine; hydroxyethyl cellulose (2000 CPS at 1%); isopropyl alcohol; edetate sodium; aloe vera leaf; DMDM hydantoin; triclosan; potassium cocoate; polyquaternium-7 (70/30 acrylamide/DADMAC; 1600 kd)

DRUMMOND AMERICAN TRADE WIND Antimicrobial Lotion Soap

Drug Facts

Active Ingredient

Chloroxylenol (1% v/v)

Purpose

Antiseptic Hand Sanitizer

Uses

- Helps reduce bacteria that potentially can cause disease
- Helps prevent cross contamination by hand contact

Warnings

- For external use only
- Do not use near eyes
- Keep out of reach of children.
- In case of eye contact flush with water for 15 minutes
- If irritation persists, get medical attention
- In case of accidental ingestion, seek medical attention or contact a poison control center immediately.

Directions

- Wet hands and forearms
- Apply appropriate amount to palm and hand
- Scrub hands and forearms for 60 seconds
- Rinse well
- Wipe dry with towel, repeat if necessary.

Other Information

- Assists with OSHA bloodborne pathogen standard compliance

Inactive Ingredients

Water, Cocoate, Oleate, Cocamidopropyl betaine, Hydroxyethyl Cellulose, Polyquaternium 7, Na4EDTA, 2-Propanol, Peg-75 Lanolin, Aloe Vera Gel, Fragrance, Triclosan, DMDM Hydantoin.

Principal Display Panel – Bottle Label

DRUMMOND AMERICAN

TRADE WIND

Antimicrobial Lotion Soap

KEEP OUT OF REACH OF CHILDREN

SEE DRUG FACTS PANEL FOR ADDITIONAL INFORMATION.

©Drummond American Corporation 1995 Reproduction in whole or in part prohibited DL3070-0505

Made & printed in U.S.A.